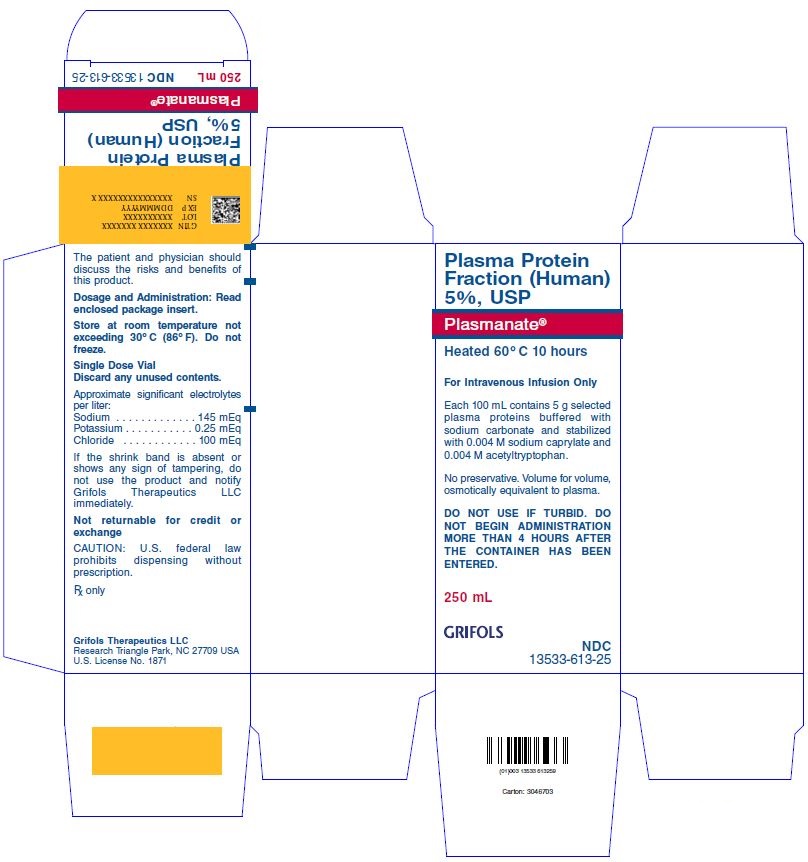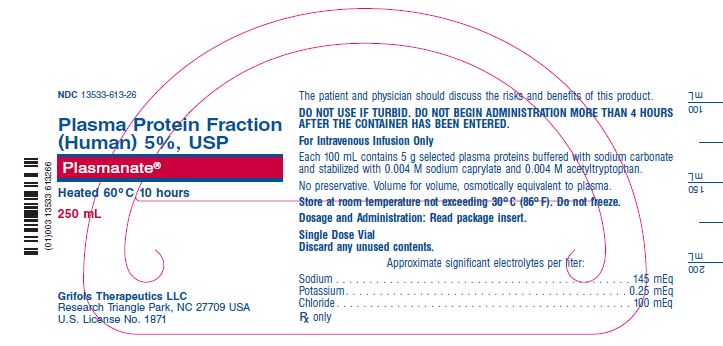 DRUG LABEL: Plasmanate 
NDC: 13533-613 | Form: SOLUTION
Manufacturer: GRIFOLS USA, LLC
Category: other | Type: PLASMA DERIVATIVE
Date: 20250405

ACTIVE INGREDIENTS: Albumin Human 2.5 g/50 mL
INACTIVE INGREDIENTS: Acetyltryptophan, Dl-; Sodium Caprylate; Water

Plasma Protein Fraction (Human) 5%, USP
Plasmanate®

DESCRIPTION

This product has been prepared from large pools of human plasma. Each 100 mL of Plasma Protein Fraction (Human) 5%, USP—Plasmanate® contains 5 g selected plasma proteins buffered with sodium carbonate and stabilized with 0.004 M sodium caprylate and 0.004 M acetyltryptophan. The plasma proteins consist of approximately 88% normal human albumin, 12% alpha and beta globulins and not more than 1% gamma globulin as determined by electrophoresis.(1) The concentration of these proteins is such that this solution is iso-oncotic with normal human plasma and is isotonic. The approximate concentrations of the significant electrolytes in Plasmanate are: sodium 145 mEq/L, potassium 0.25 mEq/L, and chloride 100 mEq/L. Plasmanate is clear and amber colored. Plasmanate must be administered intravenously.

This product is designed to bring to the medical profession a preparation derived from human blood and similar to human plasma. Each vial of Plasmanate is sterile and heat-treated at 60°C for 10 hours against the possibility of transmitting the hepatitis viruses.

The blood group agglutinins and agglutinogens A and B are at such a low level in Plasmanate solution that its use has no effect on routine blood typing procedures. No chemical or microscopic alterations of the urine have been observed with its use.

Additionally, the manufacturing process was investigated for its capacity to decrease the infectivity of an experimental agent of transmissible spongiform encephalopathy (TSE), considered as a model for the variant Creutzfeldt-Jakob disease (vCJD) and Creutzfeldt-Jakob disease (CJD) agents. (5-8) The production steps from Pooled Plasma to Effluent IV-1 in the Plasmanate manufacturing process have been shown to decrease TSE infectivity of that experimental model agent (a total of ≥7.0 logs). These studies provide reasonable assurance that low levels of vCJD/CJD agent infectivity, if present in the starting material, would be removed.

CLINICAL PHARMACOLOGY

In normal human volunteers, Plasmanate has resulted in an increased blood volume which has lasted up to 48 hours.(2) Clinical experience has indicated that it is an adequate replacement for human plasma in the treatment of shock and is a suitable means of providing human proteins for their osmotic effect.

INDICATIONS AND USAGE

Treatment of Shock — Plasmanate is indicated in the treatment of shock due to burns, crushing injuries, abdominal emergencies, and any other cause where there is a predominant loss of plasma fluids and not red blood cells. It is also effective in the emergency treatment of shock due to hemorrhage.(3,4) Following the emergency phase of therapy, blood transfusions may be indicated depending on the severity of the blood loss.

In infants and small children, Plasmanate has been found to be very useful in the initial therapy of shock due to dehydration and infection.

CONTRAINDICATIONS

Plasmanate is contraindicated for use in patients on cardiopulmonary bypass. Severe hypotension has been reported in such patients when given Plasma Protein Fraction.(4)

Plasma Protein Fraction is contraindicated in patients with severe anemia, congestive heart failure, or increased blood volume.

WARNINGS

Plasmanate is made from human plasma. Products made from human plasma may contain infectious agents, such as viruses, and, theoretically, the Creutzfeldt-Jakob Disease (CJD) agent that can cause disease. The risk that such products will transmit an infectious agent has been reduced by screening plasma donors for prior exposure to certain viruses, by testing for the presence of certain current virus infections, and by inactivating and/or removing certain viruses. Despite these measures, such products can still potentially transmit disease. There is also the possibility that unknown infectious agents may be present in such products. Individuals who receive infusions of blood or plasma products may develop signs and/or symptoms of some viral infections, particularly hepatitis C. ALL infections thought by a physician possibly to have been transmitted by this product should be reported by the physician or other healthcare provider to Grifols Therapeutics LLC [1-800-520-2807].

The physician should discuss the risks and benefits of this product with the patient, before prescribing or administering it to the patient.

Solutions which are turbid or which have been frozen should not be used. Do not use if turbid. Do not begin administration more than 4 hours after the container has been entered. Partially used vials must be discarded. Vials which are cracked or which have been previously entered or damaged should not be used, as this may have allowed the entry of microorganisms. Plasma Protein Fraction (Human) 5%, USP—Plasmanate®contains no preservative.

PRECAUTIONS

General

Rapid infusion of Plasmanate (greater than 10mL/minute) has produced hypotension in patients undergoing surgery or in the preoperative or postoperative period. Blood pressure should be monitored during use and infusion slowed or ceased if sudden hypotension occurs.

Plasmanate does not provide coagulation factors and therefore does not correct coagulation disorders.

Drug Interactions

Plasmanate is compatible with whole blood, packed red cells as well as the standard carbohydrate and electrolyte solutions intended for intravenous use. It should, however, not be mixed with protein hydrolysates or solutions containing alcohol.

Pregnancy

Animal reproduction studies have not been conducted with Plasmanate. It is also not known if Plasmanate can cause fetal harm when administered to a pregnant woman or can affect reproduction capacity. Plasmanate should be given to a pregnant woman only if clearly needed.

Pediatric Use

Safety and effectiveness in the pediatric population have not been established.

ADVERSE REACTIONS

Hypotension may occur, particularly following rapid infusion or intraarterial administration to patients on cardiopulmonary bypass. The blood pressure may normalize spontaneously after the slowing or discontinuation of the infusion. Vasopressors will also correct the hypotension.

Flushing, urticaria, back pain, nausea and headache have been occasionally reported by conscious patients.

DOSAGE AND ADMINISTRATION

Dosage is based almost entirely on the nature of the individual case and response to therapy. The usual minimum effective dose in adults is 250–500 mL. As with any plasma expander, the rate should be adjusted or slowed according to the clinical response and rising blood pressure.

Administration should be by vein and preferably through an area of skin at some distance from any site of infection or trauma. Plasmanate is compatible with the usual carbohydrate and electrolyte solutions.

Remove seal to expose stopper. Always swab stopper top immediately with suitable antiseptic prior to entering the vial.

Parenteral drug products should be inspected visually for particulate matter and discoloration prior to administration, whenever solution and container permit.

Only 16 gauge needles or dispensing pins should be used with 20 mL vial sizes and larger. Needles or dispensing pins should only be inserted within the stopper area delineated by the raised ring. The stopper should be penetrated perpendicular to the plane of the stopper within the ring.

A number of factors beyond our control could reduce the efficacy of this product or even result in an ill effect following its use. These include improper storage and handling of the product after it leaves our hands, diagnosis, dosage, method of administration, and biological differences in individual patients. Because of these factors, it is important that this product be stored properly and that the directions be followed carefully during use.

HOW SUPPLIED

Plasmanate is available in 50 mL pediatric size, 250 mL and 500 mL rubber-stoppered vials. Each single dose vial contains plasma protein in the following approximate amounts:

NDC Number | Size | Grams Protein
13533-613-20 | 50 mL | 2.5
13533-613-25 | 250 mL | 12.5
13533-613-27 | 500 mL | 25.0

STORAGE

Store at room temperature not exceeding 30°C (86°F). Solution that has been frozen should not be used. Do not use after expiration date.

CAUTION

Rx only

U.S. federal law prohibits dispensing without prescription.

REFERENCES

1. Hink JH Jr, Hidalgo J, Seeberg VP, Johnson FF. Preparation and properties of a heat-treated human plasma protein fraction. Vox Sang. 1957;2:174–86.
2. Bertrand JJ, Feichtmeir TV, Kolomeyer N, Beatty JO, Murphy PL, Waldschmidt WD, et al. Clinical investigations with a heat-treated plasma protein fraction—Plasmanate®. Vox Sang. 1959;4:385–402.
3. Tullis JL. Albumin. 1. Background and use. 2. Guidelines for clinical use. JAMA. 1977;237:355–60; 460–3.
4. Bland JHL, Laver MB, Lowenstein E. Vasodilator effect of commercial 5% plasma protein fraction solutions. JAMA. 1973;224:1721–4.
5. Stenland CJ, Lee DC, Brown P, Petteway SR Jr, Rubenstein R. Partitioning of human and sheep forms of the pathogenic prion protein during the purification of therapeutic proteins from human plasma. Transfusion. 2002;42:1497-500.
6. Lee DC, Stenland CJ, Miller JL, Cai K, Ford EK, Gilligan KJ, et al. A direct relationship between the partitioning of the pathogenic prion protein and transmissible spongiform encephalopathy infectivity during the purification of plasma proteins. Transfusion. 2001;41:449-55.
7. Lee DC, Stenland CJ, Hartwell RC, Ford EK, Cai K, Miller JL, et al. Monitoring plasma processing steps with a sensitive Western blot assay for the detection of the prion protein. J Virol Methods. 2000;84:77-89.
8. Cai K, Miller JL, Stenland CJ, Gilligan KJ, Hartwell RC, Terry JC, et al. Solvent-dependent precipitation of prion protein. Biochim Biophys Acta. 2002;1597:28-35.

Rev. June 2018
Grifols Therapeutics LLC
Research Triangle Park, NC 27709 USA
U.S. License No. 1871
3051852

PACKAGE LABEL

Plasma Protein Fraction (Human) 5%, USP
Plasmanate®
Heated 60ºC 10 hours
For Intravenous Infusion Only
Each 100 mL contains 5 g selected plasma proteins buffered with sodium carbonate and stabilized with 0.004 M sodium caprylate and 0.004 M acetyltryptophan.
No preservative. Volume for volume, osmotically equivalent to plasma.
DO NOT USE IF TURBID. DO NOT BEGIN ADMINISTRATION MORE THAN 4 HOURS AFTER THE CONTAINER HAS BEEN ENTERED.
250 mL
GRIFOLS
NDC 13533-613-25
The patient and physician should discuss the risks and benefits of this product.
Dosage and Administration: Read enclosed package insert.
Store at room temperature not exceeding 30ºC (86ºF). Do not freeze.
Single Dose Vial
Discard any unused contents.
Approximate significant electrolytes per liter:
Sodium . . . . . . . . . . . . . .145 mEq
Potassium . . . . . . . . . . . .0.25 mEq
Chloride . . . . . . . . . . . . . .100 mEq
If the shrink band is absent or shows any sign of tampering, do not use the product and notify Grifols Therapeutics LLC immediately.
Not returnable for credit or exchange
CAUTION: U.S. federal law prohibits dispensing without prescription.
Rx only
Grifols Therapeutics LLC
Research Triangle Park, NC 27709 USA
U.S. License No. 1871
Carton: 3046703
GTIN XXXXXXXXXXXXXX
LOT XXXXXXXXXX
EXP DDMMMYYYY
SN XXXXXXXXXXXXXXXX

NDC 13533-613-26
Plasma Protein Fraction (Human) 5%, USP
Plasmanate®
Heated 60ºC 10 hours
250 mL
Grifols Therapeutics LLC
Research Triangle Park, NC 27709 USA
U.S. License No. 1871
The patient and physician should discuss the risks and benefits of this product.
DO NOT USE IF TURBID. DO NOT BEGIN ADMINISTRATION MORE THAN 4 HOURSvAFTER THE CONTAINER HAS BEEN ENTERED.
For Intravenous Infusion Only
Each 100 mL contains 5 g selected plasma proteins buffered with sodium carbonate and stabilized with 0.004 M sodium caprylate and 0.004 M acetyltryptophan.
No preservative. Volume for volume, osmotically equivalent to plasma.
Store at room temperature not exceeding 30ºC (86ºF). Do not freeze.
Dosage and Administration: Read package insert.
Single Dose Vial
Discard any unused contents.
Approximate significant electrolytes per liter:
Sodium . . . . . . . . . . . . . . . . . . . . . . . . . . . . . . . . . . . . . . . . . . . . 145 mEq
Potassium. . . . . . . . . . . . . . . . . . . . . . . . . . . . . . . . . . . . . . . . . . 0.25 mEq
Chloride. . . . . . . . . . . . . . . . . . . . . . . . . . . . . . . . . . . . . . . . . . . . 100 mEq
Rx only
3051826
Lot
Exp.